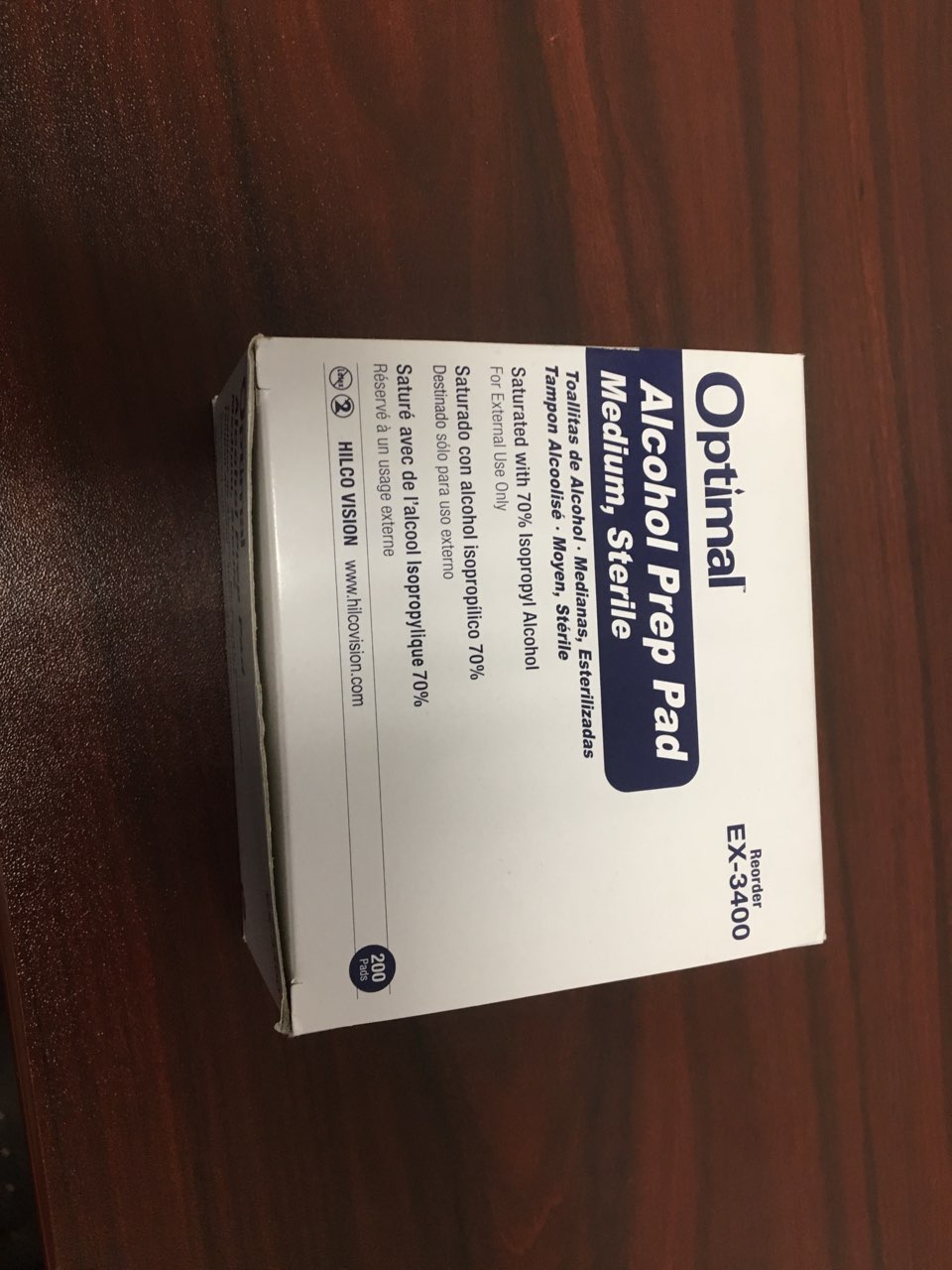 DRUG LABEL: Optimal Alcohol Prep Pad
NDC: 72347-070 | Form: SWAB
Manufacturer: Hilco Vision
Category: otc | Type: HUMAN OTC DRUG LABEL
Date: 20180628

ACTIVE INGREDIENTS: ISOPROPYL ALCOHOL 70 g/100 g
INACTIVE INGREDIENTS: WATER

Active Ingredient

Isopropyl Alcohol 70%

Purpose

Antiseptic Cleanser

INDICATIONS AND USAGE

Apply topically as needed to cleanse

Warnings

For external use only. Flammable, keep away from fire or flame.

Do Not Use

With electrocautery procedures. In the eyes. If contact occurs, flush eyes with water.

Stop Use

If irritation and redness develop. If condtion persists consult your health care practitioner.

Keep Out of Reach of Children

if swallowed get medical help or contact a Poison Control Center right away.

Other Information

Store at room temperature 15°-30° C (59°-86° F)

Inactive Ingredient

Purified water

DOSAGE AND ADMINISTRATION

For External Use Only